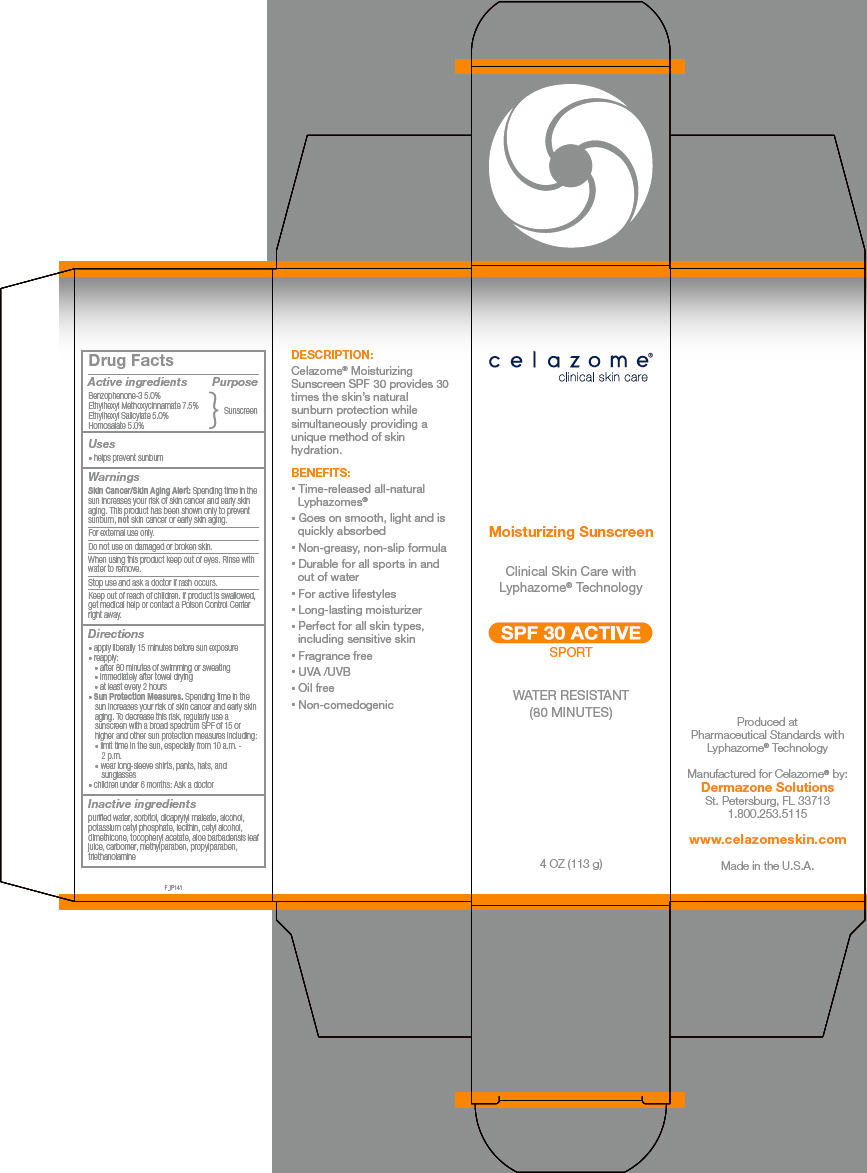 DRUG LABEL: celazome
NDC: 58466-901 | Form: CREAM
Manufacturer: Dermazone LLC
Category: otc | Type: HUMAN OTC DRUG LABEL
Date: 20250725

ACTIVE INGREDIENTS: OXYBENZONE 50 mg/1 g; OCTINOXATE 75 mg/1 g; OCTISALATE 50 mg/1 g; HOMOSALATE 50 mg/1 g
INACTIVE INGREDIENTS: WATER; DIOCTYL MALEATE; ALCOHOL; SORBITOL; DIETHANOLAMINE CETYL PHOSPHATE; ALOE VERA LEAF; .ALPHA.-TOCOPHEROL ACETATE; DIMETHICONE, UNSPECIFIED; CETYL ALCOHOL; TROLAMINE; PROPYLPARABEN; METHYLPARABEN

celazome®
Moisturizing SPF 30 Active

Drug Facts

Active ingredients

Benzophenone-3 5.0%
Ethylhexyl Methoxycinnamate 7.5%
Ethylhexyl Salicylate 5.0%
Homosalate 5.0%

Purpose

Sunscreen

Uses

- helps prevent sunburn

Warnings

Skin Cancer/Skin Aging Alert

Spending time in the sun increases your risk of skin cancer and early skin aging. This product has been shown only to prevent sunburn, not skin cancer or early skin aging.

For external use only.

Do not use on damaged or broken skin.

When using this product keep out of eyes. Rinse with water to remove.

Stop use and ask a doctor if rash occurs.

Keep out of reach of children. If product is swallowed, get medical help or contact a Poison Control Center right away.

Directions

- apply liberally 15 minutes before sun exposure
- reapply:
  - after 80 minutes of swimming or sweating
  - immediately after towel drying
  - at least every 2 hours
- Sun Protection Measures. Spending time in the sun increases your risk of skin cancer and early skin aging. To decrease this risk, regularly use a sunscreen with a broad spectrum SPF of 15 or higher and other sun protection measures including:
  - limit time in the sun, especially from 10 a.m. - 2 p.m.
  - wear long-sleeve shirts, pants, hats, and sunglasses
- children under 6 months: Ask a doctor

Inactive ingredients

purifed water, sorbitol, dicaprylyl maleate, alcohol, potassium cetyl phosphate, lecithin, cetyl alcohol, dimethicone, tocopheryl acetate, aloe barbadensis leaf juice, carbomer, methylparaben, propylparaben, triethanolamine

Manufactured for Celazome® by:
Dermazone Solutions
St. Petersburg, FL 33713

PRINCIPAL DISPLAY PANEL - 113 g Bottle Carton

celazome®
clinical skin care

Moisturizing Sunscreen

Clinical Skin Care with
Lyphazome® Technology

SPF 30 ACTIVE
SPORT

WATER RESISTANT
(80 MINUTES)

4 OZ (113 g)